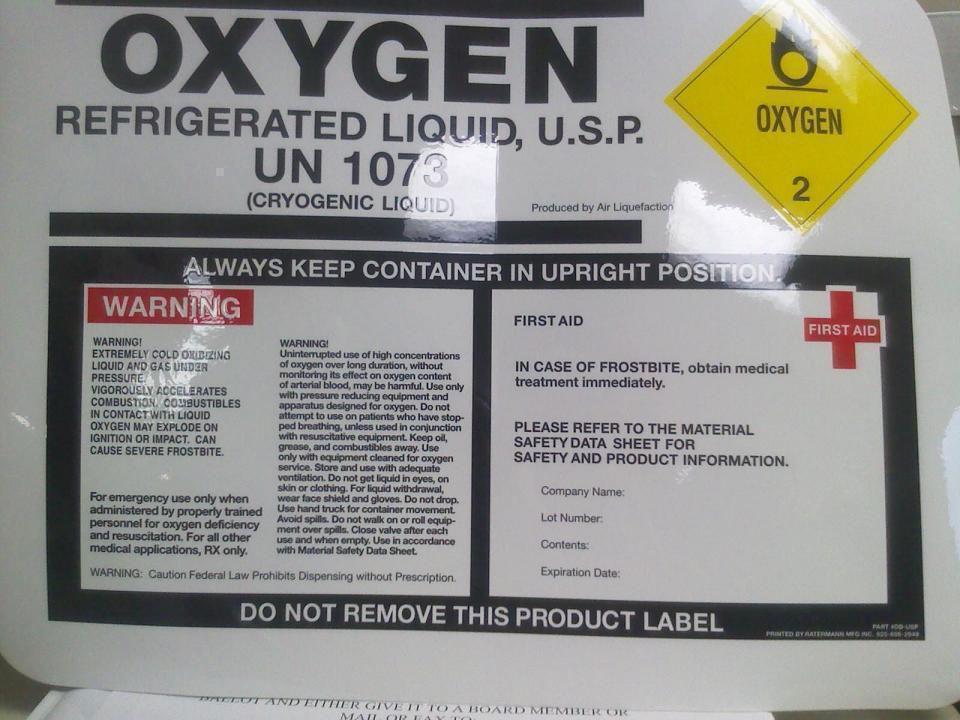 DRUG LABEL: oxygen
NDC: 50975-011 | Form: GAS
Manufacturer: Fox Welding Supply Inc
Category: prescription | Type: HUMAN PRESCRIPTION DRUG LABEL
Date: 20140416

ACTIVE INGREDIENTS: oxygen 990 mL/1 L

Oxygen Label

PACKAGE LABEL

OXYGEN REFRIGERATED LIQUID, USP UN 1073
(CRYOGENIC LIQUID) Produced by Air Liquefaction
ALWAYS KEP CONTAINER IN UPRIGHT POSITION.
WARNING
WARNING: EXTREMELY COLD OXIDIZING LIQDUI AND GAS UNDER PRESSURE. VIGOROUSLY ACCELERATED COMBUSTION. COMBUSTIBLES IN CONTACT WITH LIQUID OXYGEN MAY EXPLODE ON IGNITION OR IMPACT. CAN CAUSE SEVERE FROSTBITE.
For emergency use only when administered b properly trained personnel for xogyen deficiency and resuscitation. For all other medical applications, RX only.
WARNING: Uninterrupted use of high concentrations of oxygen over long diruation, without monitoring its effects on oxygen content in arerial blood, may be harmful. Use only with pressure reducing equipment, and apparatus designed for oxygen. Do not attempt to use on patients who have stopped breathing, unless used in conjunction with resuscitative equipment. Keep oil, grease and combustibles away. Use only with equipment cleaned for oxygen service. Store and use with adequate ventilation. Do not get liquid in eyes, on skin or clothing. For liquid withdrawal, wear face shield and gloves. Do not drop. Use hand truck for container movement. Avoid spills. Do not walk on or roll equipment over spills. Close valve after each use and when empty. Use in accordance with Material Safety Data Sheet.
DO NOT REMOVE THIS PRODUCT LABEL.
FIRST AID
IN CASE OF FROSTBITE, obtain medical treatment immediately.
PLEASE REFER TO THE MATERIAL SAFETY DATA SHEET FOR SAFETY AND PRODUCT INFORMATION
Company Name:
Lot Number:
Contents:
Expiration Date:
WARNING: Caution Federal Law Prohibits Dispensing without Prescription.